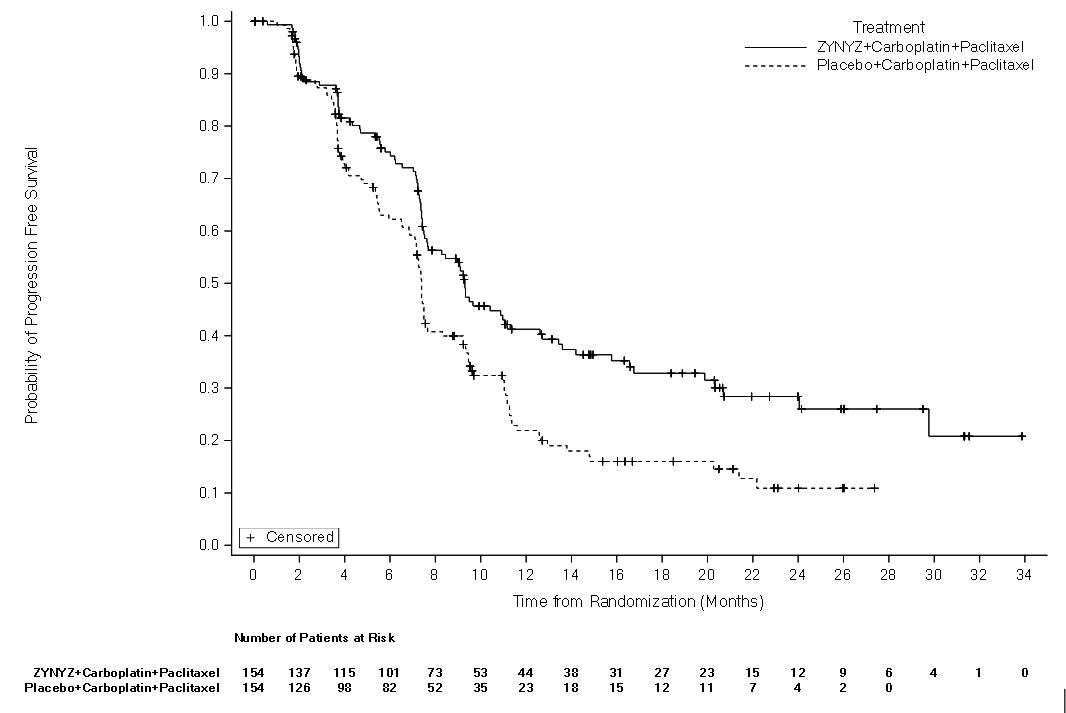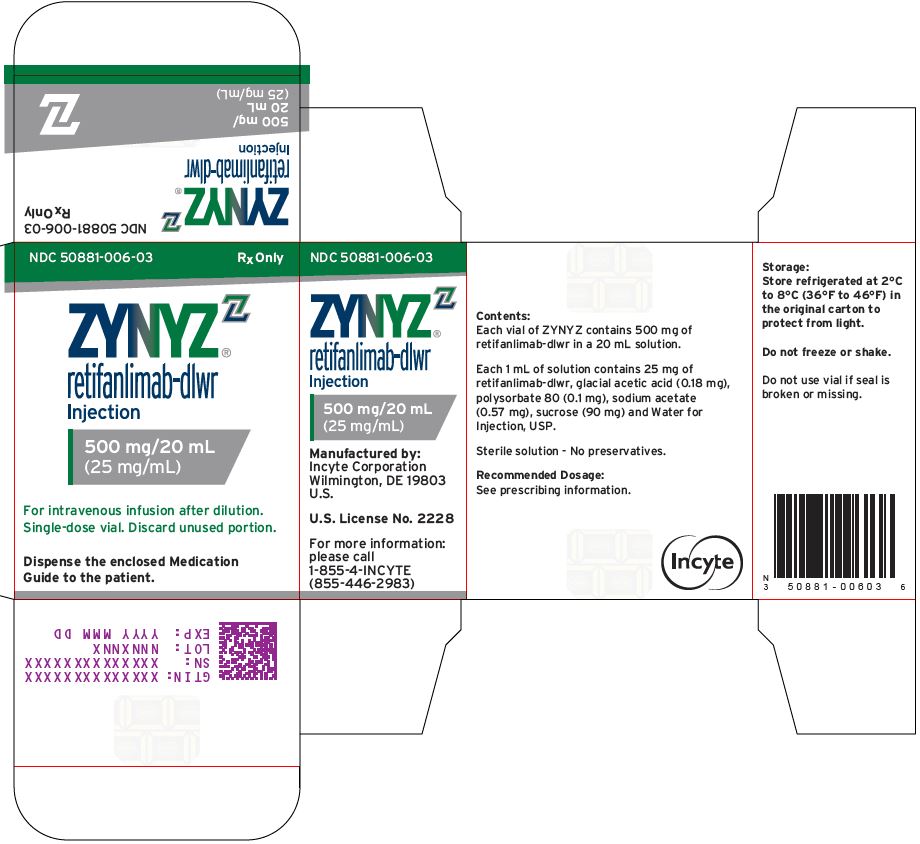 DRUG LABEL: ZYNYZ
NDC: 50881-006 | Form: INJECTION
Manufacturer: Incyte Corporation
Category: prescription | Type: HUMAN PRESCRIPTION DRUG LABEL
Date: 20260106

ACTIVE INGREDIENTS: RETIFANLIMAB 25 mg/1 mL
INACTIVE INGREDIENTS: SODIUM ACETATE .95 mg/1 mL; ACETIC ACID .18 mg/1 mL; SUCROSE 90 mg/1 mL; POLYSORBATE 80 .1 mg/1 mL; WATER

HIGHLIGHTS OF PRESCRIBING INFORMATION

These highlights do not include all the information needed to use ZYNYZ safely and effectively. See full prescribing information for ZYNYZ.
ZYNYZ® (retifanlimab-dlwr) injection, for intravenous use
Initial U.S. Approval: 2023

RECENT MAJOR CHANGES

Indications and Usage (1.1) | 5/2025
Indications and Usage (1.2) | 12/2025
Dosage and Administration (2.1) | 5/2025
Warnings and Precautions (5.1) | 5/2025

1 INDICATIONS AND USAGE

ZYNYZ is a programmed death receptor-1 (PD-1)–blocking antibody indicated:

Squamous Cell Carcinoma of the Anal Canal (SCAC)

- in combination with carboplatin and paclitaxel for the first-line treatment of adult patients with inoperable locally recurrent or metastatic squamous cell carcinoma of the anal canal (SCAC). (1.1)
- as a single agent for the treatment of adult patients with locally recurrent or metastatic SCAC with disease progression on or intolerance to platinum-based chemotherapy. (1.1)

Merkel Cell Carcinoma (MCC)

- for the treatment of adult patients with metastatic or recurrent locally advanced Merkel cell carcinoma (MCC). (1.2)

2 DOSAGE AND ADMINISTRATION

The recommended dosage of ZYNYZ is 500 mg as an intravenous infusion over 30 minutes every 4 weeks. (2.1)

See full prescribing information for dosage modifications for adverse reactions (2.2) and preparation and administration instructions. (2.3)

3 DOSAGE FORMS AND STRENGTHS

Injection: 500 mg/20 mL (25 mg/mL) solution in a single-dose vial. (3)

4 CONTRAINDICATIONS

None. (4)

5 WARNINGS AND PRECAUTIONS

- Immune-Mediated Adverse Reactions (5.1)
  - Immune-mediated adverse reactions, which may be severe or fatal, can occur in any organ system or tissue, including the following: immune-mediated pneumonitis, immune-mediated colitis, immune‑mediated hepatitis, immune-mediated endocrinopathies, immune-mediated nephritis with renal dysfunction, and immune‑mediated dermatologic adverse reactions, and solid organ transplant rejection.
  - Monitor for early identification and management. Evaluate liver enzymes, creatinine, and thyroid function at baseline and periodically during treatment.
  - Withhold or permanently discontinue ZYNYZ and administer corticosteroids based on the severity of reaction. (2.2)
- Infusion-Related Reactions: Interrupt, slow the rate of infusion, or permanently discontinue ZYNYZ based on severity of reaction. (2.2, 5.2)
- Complications of Allogeneic HSCT: Fatal and other serious complications can occur in patients who receive allogeneic HSCT before or after being treated with a PD‑1/PD‑L1–blocking antibody. (5.3)
- Embryo-Fetal Toxicity: Can cause fetal harm. Advise females of reproductive potential of the potential risk to a fetus and use of effective contraception. (5.4, 8.1, 8.3)

6 ADVERSE REACTIONS

ZYNYZ in Combination with Carboplatin and Paclitaxel

- In patients with SCAC, the most common (≥ 20%) adverse reactions are fatigue, peripheral neuropathy, nausea, alopecia, diarrhea, musculoskeletal pain, constipation, hemorrhage, rash, vomiting, decreased appetite, pruritus, and abdominal pain. (6.1)

ZYNYZ as a Single Agent

- In patients with SCAC, the most common (≥ 10%) adverse reactions are fatigue, musculoskeletal pain, diarrhea, non-urinary tract infections, perineal pain, hemorrhage, urinary tract infection, rash, nausea, decreased appetite, constipation, abdominal pain, dyspnea, pyrexia, vomiting, cough, pruritus, hypothyroidism, headache, and decreased weight. (6.1)
- In patients with MCC, the most common (≥ 10%) adverse reactions are musculoskeletal pain, fatigue, pruritus, diarrhea, rash, pyrexia, nausea, and constipation. (6.1)

To report SUSPECTED ADVERSE REACTIONS, contact Incyte Corporation at 1-855-463-3463 or FDA at 1-800-FDA-1088 or www.fda.gov/medwatch.

8 USE IN SPECIFIC POPULATIONS

Lactation: Advise not to breastfeed. (8.2)

FULL PRESCRIBING INFORMATION

1 INDICATIONS AND USAGE

1.1 Squamous Cell Carcinoma of the Anal Canal

- ZYNYZ, in combination with carboplatin and paclitaxel, is indicated for the first-line treatment of adult patients with inoperable locally recurrent or metastatic squamous cell carcinoma of the anal canal (SCAC).
- ZYNYZ, as a single agent, is indicated for the treatment of adult patients with locally recurrent or metastatic SCAC with disease progression on or intolerance to platinum‑based chemotherapy.

1.2 Merkel Cell Carcinoma

ZYNYZ is indicated for the treatment of adult patients with metastatic or recurrent locally advanced Merkel cell carcinoma (MCC).

2 DOSAGE AND ADMINISTRATION

2.1 Recommended Dosage

The recommended dosages of ZYNYZ are provided in Table 1.

Administer ZYNYZ as an intravenous infusion after dilution, over 30 minutes, as recommended [see Dosage and Administration (2.3)].

Table 1: Recommended Dosage of ZYNYZ
Indication | Recommended Dosage of ZYNYZ | Duration of Treatment
Combination Therapy [Refer to the Prescribing Information for the agents administered in combination with ZYNYZ for recommended dosing information, as appropriate.]
Adult patients with inoperable locally recurrent or metastatic SCAC in combination with carboplatin and paclitaxel | 500 mg every 4 weeks | Until disease progression, unacceptable toxicity, or up to 12 months
Monotherapy
Adult patients with locally recurrent or metastatic SCAC with disease progression on or intolerance to platinum-based chemotherapy | 500 mg every 4 weeks | Until disease progression, unacceptable toxicity, or up to 24 months
Adult patients with metastatic or recurrent locally advanced MCC | 500 mg every 4 weeks | Until disease progression, unacceptable toxicity, or up to 24 months

2.2 Dosage Modifications for Adverse Reactions

No dose reduction of ZYNYZ is recommended. In general, withhold ZYNYZ for severe (Grade 3) immune-mediated adverse reactions. Permanently discontinue ZYNYZ for life‑threatening (Grade 4) immune-mediated adverse reactions, recurrent severe (Grade 3) immune-mediated reactions that require systemic immunosuppressive treatment, or an inability to reduce corticosteroid dose to 10 mg or less of prednisone equivalent per day within 12 weeks of initiating steroids.

Dosage modifications for ZYNYZ for adverse reactions that require management different from these general guidelines are summarized in Table 2.

Table 2: Recommended Dosage Modifications for Adverse Reactions
Adverse Reaction | Severity [Toxicity graded per National Cancer Institute (NCI) Common Terminology Criteria for Adverse Events (CTCAE) v5.] | ZYNYZ Dosage Modifications
Immune-Mediated Adverse Reactions [see Warnings and Precautions (5.1)]
Pneumonitis | Grade 2 | Withhold [Resume in patients with complete or partial resolution (Grade 0 to 1) after corticosteroid taper. Permanently discontinue if no resolution within 12 weeks of initiating steroids or inability to reduce prednisone to less than 10 mg/day (or equivalent) within 12 weeks of initiating steroids.]
Pneumonitis | Grade 3 or 4 | Permanently discontinue
Colitis | Grade 2 or 3 | Withhold
Colitis | Grade 4 | Permanently discontinue
Hepatitis with no tumor involvement of the liver | AST or ALT greater than 3 but no more than 8 times ULN; OR; Total bilirubin increases to more than 1.5 and up to 3 times ULN | Withhold
Hepatitis with no tumor involvement of the liver | AST or ALT increases to more than 8 times ULN; OR; Total bilirubin greater than 3 times ULN | Permanently discontinue
Hepatitis with tumor involvement of the liver [If AST and ALT are less than or equal to ULN at baseline in patients with liver involvement, withhold or permanently discontinue ZYNYZ based on recommendations for hepatitis with no liver involvement.] | Baseline AST or ALT is more than 1 and up to 3 times ULN and increases more than 5 and up to 10 times ULN; OR; Baseline AST or ALT is more than 3 and up to 5 times ULN and increases more than 8 and up to 10 times ULN | Withhold
Hepatitis with tumor involvement of the liver [If AST and ALT are less than or equal to ULN at baseline in patients with liver involvement, withhold or permanently discontinue ZYNYZ based on recommendations for hepatitis with no liver involvement.] | AST or ALT increases to more than 10 times ULN; OR; Total bilirubin increases to more than 3 times ULN | Permanently discontinue
Endocrinopathies [Depending on clinical severity, consider withholding for Grade 2 endocrinopathy until symptom improvement with hormone replacement. Resume once acute symptoms have resolved.] | Grade 3 or 4 | Withhold until clinically stable or permanently discontinue depending on severity
Nephritis with renal dysfunction | Grade 2 or 3 increased blood creatinine | Withhold
Nephritis with renal dysfunction | Grade 4 increased blood creatinine | Permanently discontinue
Exfoliative dermatologic conditions | Grade 3 or suspected SJS, TEN, or DRESS | Withhold
Exfoliative dermatologic conditions | Grade 4 or confirmed SJS, TEN, or DRESS | Permanently discontinue
Myocarditis | Grade 2, 3, or 4 | Permanently discontinue
Neurological toxicities | Grade 2 | Withhold
Neurological toxicities | Grade 3 or 4 | Permanently discontinue
Other Adverse Reactions
Infusion-related reactions [see Warnings and Precautions (5.2)] | Grade 1 or 2 | Interrupt or slow the rate of infusion
Infusion-related reactions [see Warnings and Precautions (5.2)] | Grade 3 or 4 | Permanently discontinue
AST = aspartate aminotransferase; ALT = alanine aminotransferase; DRESS = drug rash with eosinophilia and systemic symptoms; SJS = Stevens-Johnson syndrome; TEN = toxic epidermal necrolysis; ULN = upper limit of normal.

2.3 Preparation and Administration

Visually inspect the vial for particulate matter and discoloration prior to administration. ZYNYZ is a clear to slightly opalescent, colorless to pale yellow solution and is free of particles. Discard the vial if the solution is cloudy, discolored, or contains particulate matter.

Do not shake the vial.

Preparation

1. Withdraw 20 mL (500 mg) of ZYNYZ from one vial and discard vial with any unused portion.
2. Dilute ZYNYZ with either 0.9% Sodium Chloride Injection or 5% Dextrose Injection to a final concentration between 1.4 mg/mL and 10 mg/mL. Use polyvinylchloride (PVC) and di-2-ethylhexyl phthalate (DEHP), polyolefin copolymer, polyolefin with polyamide, or ethylene vinyl acetate infusion bags.
3. Mix diluted solution by gentle inversion. Do not shake.
4. Visually inspect the infusion bag for particulate matter and discoloration prior to administration. Discard if the solution is discolored or contains particulate matter.

Storage of diluted ZYNYZ solution

Protect the diluted ZYNYZ solution from light during storage.

Store diluted ZYNYZ solution:

- At room temperature [up to 25°C (77°F)] for no more than 8 hours from the time of preparation to the end of the infusion.

OR

- Under refrigeration at 2°C to 8°C (36°F to 46°F) for no more than 24 hours from the time of preparation to the end of the infusion. If refrigerated, allow the diluted solution to come to room temperature prior to administration. The diluted solution must be administered within 4 hours (including infusion time) once it is removed from the refrigerator.

Do not freeze or shake diluted solution.

Administration

- Administer diluted ZYNYZ solution by intravenous infusion over 30 minutes through a polyethylene, polyurethane, or PVC with DEHP intravenous line containing a sterile, non‑pyrogenic, low-protein binding polyethersulfone, polyvinylidene fluoride, or cellulose acetate 0.2 micron to 5 micron in-line or add-on filter or 15 micron mesh in-line or add-on filter. Do NOT administer ZYNYZ as an intravenous push or bolus injection.
- Do not co‑administer other drugs through the same infusion line.

3 DOSAGE FORMS AND STRENGTHS

Injection: 500 mg/20 mL (25 mg/mL), clear to slightly opalescent, colorless to pale yellow solution in a single-dose vial.

4 CONTRAINDICATIONS

None.

5 WARNINGS AND PRECAUTIONS

5.1 Severe and Fatal Immune-Mediated Adverse Reactions

ZYNYZ is a monoclonal antibody that belongs to a class of drugs that binds to either the programmed death receptor-1 (PD-1) or the PD-ligand 1 (PD-L1), blocking the PD-1/PD-L1 pathway, thereby removing inhibition of the immune response with the potential for breaking of peripheral tolerance and induction of immune-mediated adverse reactions. Important immune‑mediated adverse reactions listed under Warnings and Precautions may not be inclusive of all possible severe and fatal immune-mediated reactions.

Immune-mediated adverse reactions, which may be severe or fatal, can occur in any organ system or tissue. Immune-mediated adverse reactions can occur at any time after starting treatment with a PD-1/PD-L1–blocking antibody. While immune-mediated adverse reactions usually manifest during treatment with PD-1/PD-L1–blocking antibodies, immune-mediated adverse reactions can also manifest after discontinuation of PD-1/PD-L1–blocking antibodies. Immune-mediated adverse reactions affecting more than one body system can occur simultaneously.

Early identification and management of immune‐mediated adverse reactions are essential to ensure safe use of PD-1/PD-L1–blocking antibodies. Monitor patients closely for symptoms and signs that may be clinical manifestations of underlying immune-mediated adverse reactions. Evaluate liver enzymes, creatinine, and thyroid function at baseline and periodically during treatment. In cases of suspected immune-mediated adverse reactions, initiate appropriate workup to exclude alternative etiologies, including infection. Institute medical management promptly, including specialty consultation as appropriate.

Withhold or permanently discontinue ZYNYZ depending on severity [see Dosage and Administration (2.2)]. In general, if ZYNYZ requires interruption or discontinuation, administer systemic corticosteroid therapy (1 to 2 mg/kg/day prednisone or equivalent) until improvement to Grade 1 or less. Upon improvement to Grade 1 or less, initiate corticosteroid taper and continue to taper over at least 1 month. Consider administration of other systemic immunosuppressants in patients whose immune-mediated adverse reactions are not controlled with corticosteroids.

Toxicity management guidelines for adverse reactions that do not necessarily require systemic steroids (e.g., endocrinopathies and dermatologic reactions) are discussed below.

Immune-Mediated Pneumonitis

ZYNYZ can cause immune-mediated pneumonitis. In patients treated with other PD-1/PD-L1–blocking antibodies, the incidence of pneumonitis is higher in patients who have received prior thoracic radiation.

Immune-mediated pneumonitis occurred in 3.1% (14/452) of patients receiving ZYNYZ, including 1 (0.2%) patient with fatal pneumonitis, Grade 3 (0.9%), and Grade 2 (1.3%). Pneumonitis led to permanent discontinuation of ZYNYZ in 1 patient and withholding of ZYNYZ in 1.1% of patients. Systemic corticosteroids were required in 71% (10/14) of patients with pneumonitis. Pneumonitis resolved in 11 of the 14 patients. Of the 5 patients in whom ZYNYZ was withheld for pneumonitis, 4 reinitiated ZYNYZ after symptom improvement; of these, 1 had recurrence of pneumonitis.

Immune-Mediated Colitis

ZYNYZ can cause immune-mediated colitis. Cytomegalovirus infection/reactivation have occurred in patients with corticosteroid-refractory immune-mediated colitis treated with PD-1/PD-L1–blocking antibodies. In cases of corticosteroid-refractory colitis, consider repeating infectious workup to exclude alternative etiologies.

ZYNYZ as a Single Agent: Immune-mediated colitis occurred in 2.7% (12/452) of patients receiving ZYNYZ, including Grade 4 (0.2%), Grade 3 (0.4%), and Grade 2 (1.1%). Colitis led to permanent discontinuation of ZYNYZ in 0.9% of patients and withholding of ZYNYZ in 1.3% of patients. Systemic corticosteroids were required in 75% (9/12) of patients. Colitis resolved in 8 of the 12 patients. Of the 6 patients in whom ZYNYZ was withheld for colitis, 1 reinitiated ZYNYZ after symptom improvement; this patient did not have recurrence of colitis.

ZYNYZ in Combination with Carboplatin and Paclitaxel: Immune-mediated colitis occurred in 10% (16/154) of patients receiving ZYNYZ in combination with carboplatin and paclitaxel, including Grade 4 (0.6%), Grade 3 (2.6%), and Grade 2 (3.2%). Colitis led to permanent discontinuation of ZYNYZ in 2 patients and withholding of ZYNYZ in 2 patients. Systemic corticosteroids were required in 94% (15/16) of patients. Colitis resolved in 15 of the 16 patients. Of the 2 patients in whom ZYNYZ was withheld for colitis, both reinitiated ZYNYZ after symptom improvement; neither patient had a recurrence of colitis.

Immune-Mediated Hepatitis

ZYNYZ can cause immune-mediated hepatitis.

Immune-mediated hepatitis occurred in 3.5% (16/452) of patients receiving ZYNYZ, including Grade 4 (0.2%), Grade 3 (2.4%), and Grade 2 (0.9%). Hepatitis led to permanent discontinuation of ZYNYZ in 1.5% of patients and withholding of ZYNYZ in 1.1% of patients.

Systemic corticosteroids were required in 81% (13/16) of patients. Hepatitis resolved in 9 of the 16 patients. Of the 5 patients in whom ZYNYZ was withheld for hepatitis, 3 reinitiated ZYNYZ after symptom improvement; of these, 1 had recurrence of hepatitis.

Immune-Mediated Endocrinopathies

Adrenal Insufficiency

ZYNYZ can cause primary or secondary adrenal insufficiency. For Grade 2 or higher adrenal insufficiency, initiate symptomatic treatment per institutional guidelines, including hormone replacement as clinically indicated. Withhold or permanently discontinue ZYNYZ depending on severity [see Dosage and Administration (2.2)].

ZYNYZ as a Single Agent: Adrenal insufficiency occurred in 0.9% (4/452) of patients receiving ZYNYZ, including Grade 3 (0.4%) and Grade 2 (0.4%). Adrenal insufficiency did not lead to permanent discontinuation of ZYNYZ. ZYNYZ was withheld for 1 patient with adrenal insufficiency. All patients required systemic corticosteroids. Adrenal insufficiency resolved in 1 of the 4 patients.

ZYNYZ in Combination with Carboplatin and Paclitaxel: Adrenal insufficiency occurred in 5.8% (9/154) of patients receiving ZYNYZ in combination with carboplatin and paclitaxel, including Grade 3 and Grade 2 (1.9% each). Adrenal insufficiency led to permanent discontinuation of ZYNYZ in 1 patient and withholding of ZYNYZ in 3 patients. All patients required systemic corticosteroids. Adrenal insufficiency resolved in 4 of the 9 patients.

Hypophysitis

ZYNYZ can cause immune-mediated hypophysitis. Hypophysitis can present with acute symptoms associated with mass effect such as headache, photophobia, or visual field cuts. Hypophysitis can cause hypopituitarism. Initiate hormone replacement as clinically indicated. Withhold or permanently discontinue ZYNYZ depending on severity [see Dosage and Administration (2.2)].

Hypophysitis occurred in 0.7% (3/452) of patients receiving ZYNYZ, including Grade 3 (0.2%) and Grade 2 (0.4%). Hypophysitis led to permanent discontinuation of ZYNYZ in 1 patient and withholding of ZYNYZ in 1 patient. All patients required systemic steroids. Hypophysitis resolved in 1 of the 3 patients.

Thyroid Disorders

ZYNYZ can cause immune-mediated thyroid disorders. Thyroiditis can present with or without endocrinopathy. Hypothyroidism can follow hyperthyroidism. Initiate hormone replacement or medical management of hyperthyroidism as clinically indicated. Withhold or permanently discontinue ZYNYZ depending on severity [see Dosage and Administration (2.2)].

Thyroiditis occurred in 0.7% (3/452, all Grade 1) of patients receiving ZYNYZ. No patients discontinued or withheld ZYNYZ due to thyroiditis. Thyroiditis resolved in 1 of the 3 patients.

Hypothyroidism

Hypothyroidism occurred in 10% (46/452) of patients receiving ZYNYZ, including Grade 2 (4.9%). No patients discontinued ZYNYZ due to hypothyroidism. Hypothyroidism led to withholding of ZYNYZ in 0.4% of patients. Systemic corticosteroids were required for 1 patient and 78% (36/46) of patients received endocrine therapy.

Hyperthyroidism

Hyperthyroidism occurred in 6% (26/452) of patients receiving ZYNYZ, including Grade 2 (2.7%). No patients discontinued ZYNYZ due to hyperthyroidism. Hyperthyroidism led to withholding of ZYNYZ in 0.4% of patients. Systemic corticosteroids were required for 15% (4/26) of patients and 50% (13/26) of patients received endocrine therapy.

Type 1 Diabetes Mellitus, Which Can Present with Diabetic Ketoacidosis

Monitor patients for hyperglycemia or other signs and symptoms of diabetes. Initiate treatment with insulin as clinically indicated. Withhold ZYNYZ depending on severity [see Dosage and Administration (2.2)].

Type 1 diabetes mellitus occurred in 0.2% (1/452) of patients receiving ZYNYZ, including Grade 3 (0.2%). This event led to ZYNYZ being withheld and did not lead to permanent discontinuation of ZYNYZ. The patient received insulin.

Immune-Mediated Nephritis with Renal Dysfunction

ZYNYZ can cause immune-mediated nephritis.

Immune-mediated nephritis occurred in 2% (9/452) of patients receiving ZYNYZ, including Grade 4 (0.4%), Grade 3 (1.1%), and Grade 2 (0.4%). Nephritis led to permanent discontinuation of ZYNYZ in 1.1% of patients and withholding of ZYNYZ in 0.7% of patients.
Systemic corticosteroids were required in 67% (6/9) of patients. Nephritis resolved in 4 of the 9 patients. Of the 3 patients in whom ZYNYZ was withheld for immune-mediated nephritis, 1 reinitiated ZYNYZ after symptom improvement and did not have recurrence of immune-mediated nephritis.

Immune-Mediated Dermatologic Adverse Reactions

ZYNYZ can cause immune-mediated rash or dermatitis. Bullous and exfoliative dermatitis, including Stevens-Johnson syndrome (SJS), drug rash with eosinophilia and systemic symptoms (DRESS), and toxic epidermal necrolysis (TEN), has occurred with PD-1/PD-L1–blocking antibodies. Topical emollients and/or topical corticosteroids may be adequate to treat mild to moderate non-exfoliative rashes. Withhold or permanently discontinue ZYNYZ depending on severity [see Dosage and Administration (2.2)].

Immune-mediated skin reactions occurred in 10% (43/452) of patients receiving ZYNYZ, including Grade 4 (0.2%), Grade 3 (1.1%), and Grade 2 (8%). Immune-mediated dermatologic adverse reactions led to permanent discontinuation of ZYNYZ in 0.7% of patients and withholding of ZYNYZ in 2.7% of patients.

Systemic corticosteroids were required in 33% (14/43) of patients. Immune-mediated dermatologic adverse reactions resolved in 72% (31/43) of patients. Of the 12 patients in whom ZYNYZ was withheld for immune-mediated dermatologic adverse reactions, 8 reinitiated ZYNYZ after symptom improvement; of these, 2 had recurrence of immune-mediated dermatologic adverse reactions.

Other Immune-Mediated Adverse Reactions

The following clinically significant immune-mediated adverse reactions occurred at an incidence of < 1% in 452 patients who received ZYNYZ [see Adverse Reactions (6.1)] or were reported with the use of other PD-1/PD-L1–blocking antibodies, including severe or fatal cases.

Cardiac/vascular: myocarditis, pericarditis, vasculitis

Gastrointestinal: pancreatitis, to include increases in serum amylase and lipase levels, gastritis, duodenitis

Musculoskeletal: myositis/polymyositis, rhabdomyolysis (and associated sequelae, including renal failure), arthritis, polymyalgia rheumatica

Neurological: meningitis, encephalitis, myelitis and demyelination, myasthenic syndrome/myasthenia gravis (including exacerbation), Guillain-Barré syndrome, nerve paresis, autoimmune neuropathy

Ocular: uveitis, iritis, and other ocular inflammatory toxicities. Some cases can be associated with retinal detachment. Various grades of visual impairment to include blindness can occur. If uveitis occurs in combination with other immune-mediated adverse reactions, consider a Vogt‑Koyanagi-Harada–like syndrome, as this may require treatment with systemic steroids to reduce the risk of permanent vision loss.

Endocrine: hypoparathyroidism

Other (Hematologic/Immune): hemolytic anemia, aplastic anemia, hemophagocytic lymphohistiocytosis, systemic inflammatory response syndrome, histiocytic necrotizing lymphadenitis (Kikuchi lymphadenitis), sarcoidosis, immune thrombocytopenic purpura, solid organ transplant rejection, other transplant (including corneal graft) rejection.

5.2 Infusion-Related Reactions

A severe infusion-related reaction (Grade 3) occurred in 5 (0.8%) of 606 patients receiving ZYNYZ [see Adverse Reactions (6.1)]. Monitor patients for signs and symptoms of infusion‑related reactions. Interrupt or slow the rate of infusion or permanently discontinue ZYNYZ based on severity of reaction [see Dosage and Administration (2.2)]. Consider premedication with an antipyretic and/or an antihistamine for patients who have had previous systemic reactions to infusions of therapeutic proteins.

5.3 Complications of Allogeneic HSCT

Fatal and other serious complications can occur in patients who receive allogeneic hematopoietic stem cell transplantation (HSCT) before or after being treated with a PD-1/PD-L1–blocking antibody. Transplant-related complications include hyperacute graft-versus-host disease (GVHD), acute GVHD, chronic GVHD, hepatic veno-occlusive disease after reduced intensity conditioning, and steroid-requiring febrile syndrome (without an identified infectious cause). These complications may occur despite intervening therapy between PD-1/PD-L1 blockade and allogeneic HSCT.

Follow patients closely for evidence of transplant-related complications and intervene promptly. Consider the benefit versus risks of treatment with a PD-1/PD-L1–blocking antibody prior to or after an allogeneic HSCT.

5.4 Embryo-Fetal Toxicity

Based on its mechanism of action, ZYNYZ can cause fetal harm when administered to a pregnant woman. Animal studies have demonstrated that inhibition of the PD-1/PD-L1 pathway can lead to increased risk of immune-mediated rejection of the developing fetus, resulting in fetal death. Advise women of the potential risk to a fetus. Advise females of reproductive potential to use effective contraception during treatment with ZYNYZ and for 4 months after the last dose [see Use in Specific Populations (8.1, 8.3)].

6 ADVERSE REACTIONS

The following adverse reactions are described elsewhere in the labeling.

- Severe and Fatal Immune-Mediated Adverse Reactions [see Warnings and Precautions (5.1)]
- Infusion-Related Reactions [see Warnings and Precautions (5.2)]
- Complications of Allogeneic HSCT [see Warnings and Precautions (5.3)]

6.1 Clinical Trial Experience

Because clinical trials are conducted under widely varying conditions, adverse reaction rates observed in the clinical trials of a drug cannot be directly compared to rates in the clinical trials of another drug and may not reflect the rates observed in practice.

The safety population described in Warnings and Precautions reflects exposure to ZYNYZ 500 mg as an intravenous infusion every 4 weeks in combination with carboplatin and paclitaxel in 154 patients with SCAC enrolled in the POD1UM-303 trial, and as a single agent in 94 patients with SCAC in the POD1UM-202 trial, 107 patients with MCC in the POD1UM-201 trial, and 251 patients with other solid tumors. All patients received ZYNYZ until disease progression or unacceptable toxicity; those in the POD1UM-202 and POD1UM-201 trials received ZYNYZ for up to 24 months and those in the POD1UM-303 trial received ZYNYZ for up to 12 months. The median duration of exposure of the pooled monotherapy population was 5.4 months (range: 1 day to 27 months).

Squamous Cell Carcinoma of the Anal Canal (SCAC)

Inoperable Locally Recurrent or Metastatic SCAC: ZYNYZ in Combination with Carboplatin and Paclitaxel

The safety of ZYNYZ in patients with inoperable locally recurrent or metastatic SCAC was evaluated in 154 patients enrolled in the POD1UM-303 trial [see Clinical Studies (14.1)]. Patients received ZYNYZ 500 mg or placebo intravenously every 4 weeks in combination with carboplatin and paclitaxel for 6 cycles followed by ZYNYZ 500 mg or placebo every 4 weeks until disease progression or unacceptable toxicity. Among patients who received ZYNYZ, the median duration of exposure was 7.4 months (range: 1 day to 14.6 months).

Serious adverse reactions occurred in 47% of patients receiving ZYNYZ in combination with carboplatin and paclitaxel. The most frequent serious adverse reactions (≥ 2% of patients) were sepsis (3.2%), pulmonary embolism (3.2%), diarrhea (2.6%), and vomiting (2.6%).

In patients receiving ZYNYZ in combination with carboplatin and paclitaxel, ZYNYZ was permanently discontinued due to an adverse reaction in 11% of patients. Adverse reactions that resulted in permanent discontinuation of ZYNYZ included immune-mediated enterocolitis (2 patients), warm autoimmune hemolytic anemia, hepatitis, adrenal insufficiency, blood bilirubin increased, AST increased, blood alkaline phosphatase increased, arthritis, encephalopathy, peripheral sensorimotor neuropathy, hypothyroidism, immune‑mediated cholangitis, pruritus, malaise, and rash (1 patient each).

Dosage interruptions due to an adverse reaction, excluding temporary interruptions due to infusion-related reactions, occurred in 55% of patients who received ZYNYZ in combination with carboplatin and paclitaxel. Adverse reactions that resulted in dosage interruptions in ≥ 2% of patients were neutropenia, anemia, thrombocytopenia, leukopenia, fatigue, COVID-19, and urinary tract infection.

The most common (≥ 20%) adverse reactions were fatigue, peripheral neuropathy, nausea, alopecia, diarrhea, musculoskeletal pain, constipation, hemorrhage, rash, vomiting, decreased appetite, pruritus, and abdominal pain.

Table 3 and Table 4 summarize adverse reactions and laboratory abnormalities, respectively, that occurred in POD1UM-303.

Table 3: Adverse Reactions in ≥ 10% of Patients with Inoperable Locally Recurrent or Metastatic SCAC Receiving ZYNYZ in Combination with Carboplatin and Paclitaxel with a Difference Between Arms of ≥ 5% for All Grades or ≥ 2% for Grades 3 or 4 vs Placebo in Combination with Carboplatin and Paclitaxel in POD1UM-303
 | ZYNYZ in Combination with Carboplatin and Paclitaxel (N = 154) |  | Placebo in Combination with Carboplatin and Paclitaxel (N = 152)
Adverse Reaction | All Grades (%) | Grades 3-4; (%) | All Grades (%) | Grades 3-4; (%)
Gastrointestinal disorders
Diarrhea [Includes diarrhea, colitis, and frequent bowel movements.] | 49 | 5 | 41 | 7
Stomatitis [Includes stomatitis, aphthous ulcer, cheilitis, mouth ulceration, and mucosal inflammation.] | 18 | 0 | 11 | 0
Nervous system disorders
Peripheral neuropathy [Includes peripheral neuropathy, paresthesia, peripheral sensory neuropathy, neuralgia, hypoesthesia, peripheral sensorimotor neuropathy, dysesthesia, peripheral motor neuropathy, and hyperesthesia.] | 56 | 5 | 52 | 2.6
Musculoskeletal and connective tissue disorders
Musculoskeletal pain [Includes arthralgia, arthritis, back pain, bone pain, musculoskeletal chest pain, musculoskeletal discomfort, musculoskeletal stiffness, myalgia, neck pain, non-cardiac chest pain, pain in extremity, and spinal pain.] | 40 | 2.6 | 34 | 0
Vascular disorders
Hemorrhage [Includes hemorrhage, anal hemorrhage, anal ulcer hemorrhage, conjunctival hemorrhage, epistaxis, gastrointestinal hemorrhage, genital hemorrhage, hematuria, hemoptysis, hemorrhoidal hemorrhage, lower gastrointestinal hemorrhage, lymph node hemorrhage, rectal hemorrhage, stoma site hemorrhage, tumor hemorrhage, urinary bladder hemorrhage, uterine hemorrhage, vaginal hemorrhage, and wound hemorrhage.] | 29 | 3.2 | 21 | 0
Skin and subcutaneous tissue disorders
Rash [Includes rash, eczema, dermatitis acneiform, dermatitis, rash erythematous, rash maculo-papular, rash papular, rash pustular, and rash pruritic.] | 29 | 1.3 | 16 | 0.7
Pruritus | 24 | 0.6 | 7 | 0
Endocrine disorders
Hypothyroidism | 14 | 0.6 | 3.3 | 0
Graded according to NCI CTCAE v5.0.

Table 4: Laboratory Abnormalities that Worsened from Baseline to Grade 3 or 4 Occurring in ≥ 1% of Patients with Inoperable Locally Recurrent or Metastatic SCAC Receiving ZYNYZ in Combination with Carboplatin and Paclitaxel in POD1UM-303
 | ZYNYZ in Combination with Carboplatin and Paclitaxel [The denominator used to calculate the rate varied from 142 to 153 based on the number of patients with a baseline value and at least one post-treatment value.] |  | Placebo in Combination with Carboplatin and Paclitaxel
Laboratory abnormality | All Grades (%) | Grades 3-4 (%) | All Grades (%) | Grades 3-4 (%)
Hematology
Decreased hemoglobin | 91 | 20 | 92 | 24
Decreased leukocytes | 88 | 44 | 90 | 40
Decreased neutrophils | 79 | 52 | 78 | 39
Decreased lymphocytes | 77 | 40 | 69 | 38
Decreased platelets | 55 | 6 | 52 | 4
Chemistry
Decreased albumin | 37 | 2 | 29 | 1.3
Increased alanine aminotransferase | 35 | 3.9 | 23 | 0.7
Increased aspartate aminotransferase | 26 | 3.9 | 16 | 0
Increased alkaline phosphatase | 26 | 2 | 25 | 0
Decreased potassium | 24 | 5 | 16 | 2.6
Increased calcium | 23 | 2 | 20 | 1.3
Increased lipase | 18 | 4.9 | 15 | 0.7
Increased bilirubin | 10 | 1.3 | 4.6 | 1.3
Graded according to NCI CTCAE v5.0.

Platinum-refractory Intolerant Locally Recurrent or Metastatic SCAC: ZYNYZ as a Single Agent

The safety of ZYNYZ in patients with platinum-refractory intolerant locally recurrent or metastatic SCAC was evaluated in 94 patients in the POD1UM‑202 trial [see Clinical Studies (14.1)]. Patients received ZYNYZ 500 mg intravenously every 4 weeks until disease progression, unacceptable toxicity, or up to 24 months. The median duration of exposure was 2.8 months (range: 1 day to 27.1 months).

Serious adverse reactions occurred in 40% of patients receiving ZYNYZ. The most frequent serious adverse reactions (≥ 2% of patients) were non-urinary tract infection, perineal pain, abdominal pain, anemia, hemorrhage, diarrhea, pyrexia, urinary tract infection, musculoskeletal pain, and dyspnea.

Permanent discontinuation of ZYNYZ due to an adverse reaction occurred in 4.3% of patients. These adverse reactions included diarrhea, non-urinary tract infection, perineal pain, and rash.

Dosage interruptions due to an adverse reaction occurred in 21% of patients who received ZYNYZ. Adverse reactions that resulted in dose delay in ≥ 2% of patients who received ZYNYZ were non-urinary tract infection, rash, diarrhea, abdominal pain, hemorrhage, musculoskeletal pain, pyrexia, and urinary tract infection.

The most common (≥ 10%) adverse reactions that occurred in patients receiving ZYNYZ were fatigue, musculoskeletal pain, diarrhea, non-urinary tract infections, perineal pain, hemorrhage, urinary tract infection, rash, nausea, decreased appetite, constipation, abdominal pain, dyspnea, pyrexia, vomiting, cough, pruritus, hypothyroidism, headache, and decreased weight.

Table 5 and Table 6 summarize adverse reactions and laboratory abnormalities, respectively, that occurred in POD1UM-202.

Table 5: Adverse Reactions in ≥ 10% of Patients with Platinum-Refractory Locally Recurrent or Metastatic SCAC Receiving ZYNYZ in POD1UM-202
Adverse Reaction | ZYNYZ; (N = 94)
Adverse Reaction | All Grades (%) | Grades 3-4 (%)
General disorders and administration site conditions
Fatigue [Includes fatigue and asthenia.] | 42 | 7
Pyrexia | 14 | 2.1
Musculoskeletal and connective tissue disorders
Musculoskeletal pain [Includes arthralgia, back pain, bone pain, musculoskeletal chest pain, myalgia, non-cardiac chest pain, osteoarthritis, pain in extremity, and spinal pain.] | 27 | 2.1
Gastrointestinal disorders
Diarrhea [Includes diarrhea, gastroenteritis, and immune-mediated enterocolitis.] | 23 | 2.1
Nausea | 16 | 0
Constipation | 15 | 0
Abdominal pain [Includes abdominal pain, abdominal discomfort, and abdominal pain upper.] | 14 | 3.2
Vomiting | 14 | 1.1
Infections and infestations
Non-urinary tract infections [Includes anal abscess, cellulitis, cholangitis, cholecystitis, cholecystitis acute, device related infection, herpes zoster, Lyme disease, pelvic infection, peritonitis, Pneumocystis jirovecii pneumonia, pneumonia, postoperative wound infection, pseudomonas infection, sepsis, skin infection, stoma site infection, and wound infection bacterial.] | 21 | 12
Urinary tract infection [Includes urinary tract infection, cystitis, escherichia urinary tract infection, and pyelonephritis.] | 17 | 2.1
Reproductive system and breast disorders
Perineal pain [Includes anorectal discomfort, pelvic pain, proctalgia, and vulvovaginal discomfort.] | 19 | 7
Vascular disorders
Hemorrhage [Includes epistaxis, hematochezia, hematuria, proctitis hemorrhagic, rectal hemorrhage, stoma site hemorrhage, and vaginal hemorrhage.] | 19 | 3.2
Skin and subcutaneous tissue disorders
Rash [Includes rash, dermatitis, dermatitis acneiform, eczema, erythema, palmar-plantar erythrodysesthesia syndrome, rash erythematous, and rash maculo-papular.] | 16 | 2.1
Pruritus | 12 | 0
Metabolism and nutrition disorders
Decreased appetite [Includes decreased appetite and hypophagia.] | 15 | 2.1
Respiratory, thoracic, and mediastinal disorders
Dyspnea | 14 | 3.2
Cough [Includes cough and productive cough.] | 13 | 0
Endocrine disorders
Hypothyroidism | 10 | 0
Nervous system disorders
Headache | 10 | 0
Investigations
Decreased weight | 10 | 0
Graded according to NCI CTCAE v5.0.

Table 6: Laboratory Abnormalities that Worsened from Baseline to Grade 3 or 4 Occurring in ≥ 1% of Patients with Platinum-Refractory Locally Recurrent or Metastatic SCAC Receiving ZYNYZ in POD1UM-202
Laboratory abnormality | ZYNYZ [The denominator used to calculate the rate varied from 59 to 87 based on the number of patients with a baseline value and at least one post-treatment value.]
Laboratory abnormality | All Grades (%) | Grades 3-4 (%)
Hematology
Decreased hemoglobin | 35 | 2.3
Decreased lymphocytes | 33 | 6
Chemistry
Decreased albumin | 36 | 1.2
Increased aspartate aminotransferase | 28 | 1.1
Decreased sodium | 24 | 1.2
Increased triglycerides | 19 | 3.4
Increased lipase | 17 | 1.3
Increased alanine aminotransferase | 16 | 1.1
Increased bilirubin | 8 | 2.3
Graded according to NCI CTCAE v5.0.

Merkel Cell Carcinoma (MCC)

Metastatic or Recurrent Locally Advanced MCC: ZYNYZ as a Single Agent

The safety of ZYNYZ was evaluated in 107 patients enrolled in the POD1UM-201 trial with metastatic or recurrent locally advanced MCC [see Clinical Studies (14.2)]. Patients received ZYNYZ 500 mg intravenously every 4 weeks until disease progression, unacceptable toxicity, or up to 24 months. The median duration of exposure was 10.3 months (range: 1 day to 25 months).

Serious adverse reactions occurred in 26% of patients receiving ZYNYZ. The most frequent serious adverse reactions (≥ 2% of patients) were fatigue, arrhythmia, and pneumonitis.

Permanent discontinuation of ZYNYZ due to an adverse reaction occurred in 21% of patients. These included asthenia, colitis, demyelinating polyneuropathy, diarrhea, drug hypersensitivity, eosinophilic fasciitis, hepatitis, hypophysitis, increased transaminases, infusion-related reaction, pancreatitis, polyarthritis, radiculopathy, toxic epidermal necrolysis, and tubulointerstitial nephritis (1 patient each).

Dosage interruptions due to an adverse reaction occurred in 39% of patients who received ZYNYZ. Adverse reactions or laboratory abnormalities that required dosage interruption in > 2% of patients who received ZYNYZ were increased transaminases, increased lipase, increased amylase, and pyrexia.

The most common (≥ 10%) adverse reactions that occurred in patients receiving ZYNYZ were musculoskeletal pain, fatigue, pruritus, diarrhea, rash, pyrexia, nausea, and constipation.

Table 7 and Table 8 summarize adverse reactions and laboratory abnormalities, respectively, that occurred in POD1UM-201.

Table 7: Adverse Reactions in ≥ 10% of Patients with Metastatic or Recurrent Locally Advanced MCC Receiving ZYNYZ in POD1UM-201
Adverse Reaction | ZYNYZ (N = 107)
Adverse Reaction | All Grades (%) | Grades 3-4 (%)
Musculoskeletal and connective tissue disorders
Musculoskeletal pain [Includes arthralgia, back pain, bone pain, pain in extremity, neck pain, myalgia, and musculoskeletal chest pain.] | 37 | 3
General disorders and administration site conditions
Fatigue [Includes fatigue and asthenia.] | 33 | 1
Pyrexia | 12 | 0
Skin and subcutaneous tissue disorders
Pruritus | 22 | 0
Rash [Includes rash, dermatitis, dermatitis bullous, rash erythematous, rash maculo-papular, rash papular, rash pruritic, psoriasis, and toxic epidermal necrolysis.] | 17 | 2
Gastrointestinal disorders
Diarrhea | 19 | 0
Nausea | 12 | 0
Constipation | 11 | 0
Graded according to NCI CTCAE v5.0.

Table 8: Laboratory Abnormalities that Worsened from Baseline to Grade 3 or 4 Occurring in > 1% of Patients with Metastatic or Recurrent Locally Advanced MCC Receiving ZYNYZ in POD1UM-201
 | ZYNYZ [The denominator used to calculate the rate varied from 96 to 101 based on the number of patients with a baseline value and at least one post-treatment value.]
Laboratory Abnormality | All Grades (%) | Grades 3-4 (%)
Hematology
Decreased lymphocytes | 31 | 11
Decreased neutrophils | 14 | 3
Chemistry
Increased lipase | 39 | 5
Increased aspartate aminotransferase | 28 | 3
Decreased sodium | 27 | 3
Increased alanine aminotransferase | 26 | 4
Increased alkaline phosphatase | 22 | 2
Decreased potassium | 15 | 2
Graded according to NCI CTCAE v5.0.

8 USE IN SPECIFIC POPULATIONS

8.1 Pregnancy

Risk Summary

Based on its mechanism of action, ZYNYZ can cause fetal harm when administered to a pregnant woman [see Clinical Pharmacology (12.1)]. There are no available data on the use of ZYNYZ in pregnant women. Animal studies have demonstrated that inhibition of the PD‑1/PD‑L1 pathway can lead to increased risk of immune-mediated rejection of the developing fetus resulting in fetal death (see Data). Human IgG4 immunoglobulins (IgG4) are known to cross the placenta; therefore, retifanlimab-dlwr has the potential to be transmitted from the mother to the developing fetus. Advise women of the potential risk to a fetus.

In the U.S. general population, the estimated background risk of major birth defects and miscarriage in clinically recognized pregnancies is 2% to 4% and 15% to 20%, respectively.

Data

Animal Data

Animal reproduction studies have not been conducted with ZYNYZ to evaluate its effect on reproduction and fetal development. A central function of the PD-1/PD-L1 pathway is to preserve pregnancy by maintaining maternal immune tolerance to the fetus. In murine models of pregnancy, blockade of PD-L1 signaling has been shown to disrupt tolerance to the fetus and to result in an increase in fetal loss; therefore, potential risks of administering ZYNYZ during pregnancy include increased rates of abortion or stillbirth. As reported in the literature, there were no malformations related to the blockade of PD-1/PD-L1 signaling in the offspring of these animals; however, immune-mediated disorders occurred in PD-1 and PD-L1 knockout mice. Based on its mechanism of action, fetal exposure to retifanlimab-dlwr may increase the risk of developing immune-mediated disorders or altering the normal immune response.

8.2 Lactation

Risk Summary

There is no information regarding the presence of retifanlimab-dlwr in human milk, or its effects on the breastfed child or on milk production. Maternal IgG is known to be present in human milk. The effects of local gastrointestinal exposure and limited systemic exposure in the breastfed child to ZYNYZ are unknown. Because of the potential for serious adverse reactions in breastfed children, advise women not to breastfeed during treatment and for 4 months after the last dose of ZYNYZ.

8.3 Females and Males of Reproductive Potential

ZYNYZ can cause fetal harm when administered to a pregnant woman [see Use in Specific Populations (8.1)].

Pregnancy Testing

Verify pregnancy status in females of reproductive potential prior to initiating ZYNYZ [see Use in Specific Populations (8.1)].

Contraception

Advise females of reproductive potential to use effective contraception during treatment with ZYNYZ and for 4 months after the last dose.

8.4 Pediatric Use

The safety and effectiveness of ZYNYZ have not been established in pediatric patients.

8.5 Geriatric Use

In Combination with Carboplatin and Paclitaxel

Of the 154 patients with inoperable locally recurrent or metastatic SCAC treated with ZYNYZ in combination with carboplatin and paclitaxel in POD1UM-303, 38% were 65 years or older, and 9% were 75 years or older [see Clinical Studies (14.1)]. No overall differences in safety or effectiveness were observed between these patients and younger patients.

As a Single Agent

Of the 94 patients with locally recurrent or with metastatic SCAC treated with ZYNYZ in POD1UM‑202, 49% were 65 years or older, and 11% were 75 years or older [see Clinical Studies (14.1)].

Of the 101 patients with metastatic or recurrent locally advanced MCC treated with ZYNYZ in POD1UM-201, 76% were 65 years or older, and 39% were 75 years or older [see Clinical Studies (14.2)].

Clinical studies of ZYNYZ as a single agent did not include sufficient numbers of younger adult patients to determine if patients 65 years of age and older respond differently than younger adult patients.

11 DESCRIPTION

Retifanlimab-dlwr is a programmed death receptor-1 (PD-1)–blocking antibody. Retifanlimab‑dlwr is a humanized IgG4 kappa monoclonal antibody produced in Chinese hamster ovary cells. Retifanlimab-dlwr has an approximate molecular weight of 148 kDa.

ZYNYZ (retifanlimab-dlwr) injection is a sterile, preservative-free, clear to slightly opalescent, colorless to pale yellow solution for intravenous use. The solution is free from visible particles.

Each single-dose vial contains 500 mg of retifanlimab-dlwr in 20 mL of solution. Each mL contains 25 mg of retifanlimab-dlwr, glacial acetic acid (0.18 mg), polysorbate 80 (0.1 mg), sodium acetate (0.57 mg), sucrose (90 mg), and Water for Injection, USP. The pH is 5.1.

12 CLINICAL PHARMACOLOGY

12.1 Mechanism of Action

Binding of the PD-1 ligands, PD-L1 and PD-L2, to the PD-1 receptor found on T cells, inhibits T-cell proliferation and cytokine production. Upregulation of PD-1 ligands occurs in some tumors, and signaling through this pathway can contribute to inhibition of active T-cell immune surveillance of tumors.

Retifanlimab-dlwr binds to the PD-1 receptor, blocks interaction with its ligands PD-L1 and PD‑L2, and potentiates T-cell activity.

12.2 Pharmacodynamics

The exposure-response relationship and time course of pharmacodynamic response for safety and effectiveness of retifanlimab-dlwr have not been fully characterized.

12.3 Pharmacokinetics

The pharmacokinetics of retifanlimab-dlwr were evaluated in patients with various solid tumors, including patients with SCAC and patients with MCC. Retifanlimab-dlwr exposures (maximum concentration [Cmax] and area under the curve [AUC]) increased proportionally over a dosage range from 375 mg to 750 mg (0.75- to 1.5-fold of the approved recommended dose).

Following administration of retifanlimab-dlwr at 500 mg every 4 weeks, steady-state concentrations were achieved at Cycle 6 (approximately 6 months) and systemic accumulation was 1.3-fold.

Distribution

The geometric mean volume of distribution at steady state for retifanlimab-dlwr is 6.0 L (coefficient of variation [CV]: 20%).

Elimination

The elimination half-life of retifanlimab-dlwr at steady state is 19 days (CV: 30%). Clearance of retifanlimab-dlwr after the first dose was 0.3 L/day (CV: 38%) and decreased over time by approximately 23%, resulting in a steady-state clearance of 0.23 L/day.

Specific Populations

The following factors have no clinically meaningful effect on the pharmacokinetics of retifanlimab-dlwr: age (18 to 94 years), sex, body weight (33 to 133 kg), race (White, Black, Asian), albumin level (17 to 54 g/L), Eastern Cooperative Oncology Group (ECOG) score (0 to 2), tumor burden (sum of the target lesion diameters: 0 to 360 mm), HIV status, renal function (estimated glomerular filtration rate ≥ 26 mL/min/1.73 m^2), or mild hepatic impairment (total bilirubin less than or equal to the ULN and AST greater than ULN or total bilirubin greater than ULN and less than or equal to 1.5 times ULN and any AST). The pharmacokinetics of retifanlimab-dlwr have not been studied in patients with moderate or severe hepatic impairment.

12.6 Immunogenicity

The observed incidence of anti-drug antibodies (ADAs) is highly dependent on the sensitivity and specificity of the assay. Differences in assay methods preclude meaningful comparisons of the incidence of ADAs in the studies described below with the incidence of ADAs in other studies, including those of ZYNYZ or of other retifanlimab products.

ADAs were tested in 153 patients with SCAC who received ZYNYZ in POD1UM-303 and 94 patients with SCAC who received ZYNYZ in POD1UM-202. The incidence of retifanlimab treatment-emergent ADAs was determined using a bridging enzyme-linked immunosorbent assay following a median exposure time of 226 days in POD1UM-303 and 85 days in POD1UM‑202. None of the patients in POD1UM‑303 or POD1UM-202 tested positive for retifanlimab treatment-emergent ADAs.

ADAs were tested in 106 patients with MCC who received ZYNYZ in POD1UM-201. The incidence of retifanlimab treatment-emergent ADAs was 2.8% (3/106) using a bridging enzyme‑linked immunosorbent assay following a median exposure time of 312 days. Neutralizing antibodies were detected in 2 of 3 patients with treatment-emergent ADAs. The effect of these antibodies on the pharmacokinetics, pharmacodynamics, safety, and/or effectiveness of retifanlimab products is unknown.

13 NONCLINICAL TOXICOLOGY

13.1 Carcinogenesis, Mutagenesis, Impairment of Fertility

No studies have been performed to assess the potential of retifanlimab-dlwr for carcinogenicity or genotoxicity.

In 1-month and 3-month repeat-dose toxicology studies in monkeys, there were no notable effects in the male and female reproductive organs; however, most animals in these studies were not sexually mature.

13.2 Animal Toxicology and/or Pharmacology

In animal models, inhibition of PD-L1/PD-1 signaling increased the severity of some infections and enhanced inflammatory responses. Mycobacterium tuberculosis–infected PD-1 knockout mice exhibit markedly decreased survival compared with wild-type controls, which correlated with increased bacterial proliferation and inflammatory responses in these animals. PD-1 blockade using a primate anti-PD-1 antibody was also shown to exacerbate M. tuberculosis infection in rhesus macaques. PD-L1 and PD-1 knockout mice and mice receiving PD-L1 blocking antibody have also shown decreased survival following infection with lymphocytic choriomeningitis virus.

14 CLINICAL STUDIES

14.1 Squamous Cell Carcinoma of the Anal Canal (SCAC)

ZYNYZ in Combination with Carboplatin and Paclitaxel for the Treatment of Inoperable Locally Recurrent or Metastatic SCAC

The efficacy of ZYNYZ in combination with carboplatin and paclitaxel was evaluated in study POD1UM-303/InterAACT 2 (NCT04472429), a randomized, multicenter, double-blind study in 308 patients with chemotherapy-naïve inoperable locally recurrent or metastatic SCAC. Patients with active autoimmune disease or a medical condition that required immunosuppression, severe hepatic or renal impairment, clinically significant cardiac disease, history of organ transplant, or Eastern Cooperative Oncology Group (ECOG) performance score (PS) ≥ 2 were ineligible. Patients who had not received prior systemic therapy other than a radiosensitizing agent or neoadjuvant or adjuvant therapy completed > 6 months prior to study entry were eligible, as were patients who were HIV-positive if they had an undetectable viral load, a CD4+ count ≥ 200 cells/microliter, and were receiving antiretroviral therapy. The study did not enroll patients who received prior treatment with PD-L1‑directed therapies.

Patients were randomized (1:1) to receive either:

- ZYNYZ 500 mg intravenously every 4 weeks on Day 1, carboplatin AUC of 5 on Day 1, and paclitaxel 80 mg/m^2 on Days 1, 8, and 15 for 6 cycles followed by ZYNYZ 500 mg intravenously every 4 weeks, or
- Placebo intravenously every 4 weeks on Day 1, carboplatin AUC 5 mg/mL on Day 1, and paclitaxel 80 mg/m^2 on Days 1, 8, and 15 for 6 cycles followed by placebo 500 mg intravenously every 4 weeks.

Randomization was stratified by PD-L1 expression (< 1% versus ≥ 1%), region, and extent of disease (locally recurrent versus metastatic). Treatment with ZYNYZ continued until disease progression, unacceptable toxicity, death, or withdrawal of consent, for up to 12 months. Tumor response assessments were performed every 8 weeks throughout the treatment period. Patients randomized to the placebo arm were offered ZYNYZ as a single agent at the time of disease progression.

The major efficacy outcomes were progression-free survival (PFS) as assessed by a blinded independent central review (BICR) according to Response Evaluation Criteria in Solid Tumors (RECIST) v1.1 and overall survival (OS). Additional efficacy outcome measures included objective response rate (ORR) and duration of response (DOR), as assessed by BICR.

Among the 308 patients evaluated, the median age was 62 years (range: 29-86); 72% female, 87% White, 1.6% Black, 6% Asian, 3.2% race unknown or not reported; 7% were Hispanic or Latino, 85% were not Hispanic or Latino, 8% ethnicity unknown or not reported; 55% had an ECOG performance status (PS) of 0 and 45% had an ECOG PS of 1; 3.6% were HIV-positive and 96% had unknown or negative HIV status. Thirty-five percent of patients had prior surgery, and 71% of patients had prior radiotherapy. Eighty-three percent of patients had metastatic disease at baseline. PD-L1 expression of ≥ 1% was present in 91% of tumors. Of the 199 patients with tumor tissue available for central review, 150 (75%) were positive for human papillomavirus P16 protein expression.

Efficacy results of the final analysis of PFS and interim analysis of OS are summarized in Table 9 and Figure 1. There were 69 patients (45%) from the placebo arm who received ZYNYZ as a single agent after disease progression. OS results were not statistically significant at this interim analysis.

Table 9: Efficacy Results from Study POD1UM-303/InterAACT 2
Endpoint | ZYNYZ in Combination with Carboplatin and Paclitaxel; (N = 154) | Placebo in Combination with Carboplatin and Paclitaxel; (N = 154)
Progression-free survival
Events, n (%) | 92 (60) | 110 (71)
Median (months) (95% CI) | 9.3 (7.5, 11.3) | 7.4 (7.1, 7.7)
Hazard ratio [Based on stratified Cox model.] (95% CI) | 0.63 (0.47, 0.84)
p-value [One-sided p-value based on stratified log-rank test.] | 0.0006
Overall survival
Deaths, n (%) | 53 (34) | 73 (47)
Median (months) (95% CI) | 29.2 (24.2, NE) | 23 (15.1, 27.9)
Hazard ratio (95% CI) | 0.70 (0.49, 1.01)
Objective response rate
Objective response rate (%) (95% CI) | 56 (48, 64) | 44 (36, 52)
Complete response, n (%) | 34 (22) | 21 (14)
Partial response, n (%) | 52 (34) | 47 (31)
Median duration of response, in months (95% CI) | 14.0 (8.6, 22.2) | 7.2 (5.6, 9.3)
CI = confidence interval; NE = not evaluable.

Figure 1: Kaplan-Meier Curves for PFS in POD1UM-303/InterAACT 2

Figure 1: Kaplan-Meier Curves for PFS in POD1UM-303/InterAACT 2

Study POD1UM-202: As a Single Agent for the Treatment of Platinum-refractory or Intolerant Locally Recurrent or Metastatic Squamous Cell Carcinoma of the Anal Canal

The efficacy of ZYNYZ was evaluated in study POD1UM-202 (NCT03597295), an open-label, multicenter, single-arm study in 94 patients with locally recurrent or metastatic SCAC who progressed on or were intolerant of platinum-based chemotherapy. Patients with active autoimmune disease or a medical condition that required immunosuppression or ECOG PS ≥ 2 were ineligible. Patients who were HIV-positive, had an undetectable viral load, a CD4+ count ≥ 300 cells/microliter, and were receiving antiretroviral therapy were eligible.

Patients received ZYNYZ 500 mg intravenously every 4 weeks until disease progression, unacceptable toxicity, or up to 24 months. Tumor response assessments were performed every 8 weeks throughout the treatment period.

The major efficacy outcomes were ORR and DOR as assessed by an independent central review committee (IRC) according to RECIST v1.1.

The median age of enrolled patients was 64 years (range: 37-94); 49% ≥ 65 years; 65% female, 77% White, 1.1% Black, 22% race unknown or not reported; 4.3% were Hispanic or Latino, 52% were not Hispanic or Latino, 44% ethnicity unknown or not reported; 42% had an ECOG PS of 0 and 59% had an ECOG PS of 1; 10% were HIV‑positive. Forty-six percent of patients had prior surgery and 87% of patients had prior radiotherapy. Eighty-one percent of patients had metastatic disease at baseline. Of the 58 patients with tumor tissue available for review, 54 (93%) were positive for HPV.

Efficacy results from POD1UM‑202 are summarized in Table 10.

Table 10: Efficacy Results from Study POD1UM-202
Endpoint | ZYNYZ (N = 94)
Objective Response Rate (95% CI) | 14% (8, 23)
Complete response, n (%) | 1 (1.1)
Partial response, n (%) | 12 (13)
Duration of Response
Median, months | 9.5 (4.4, NE)
Patients with DOR ≥ 6 months (95% CI) | 65% (31, 85)
Patients with DOR ≥ 12 months (95% CI) | 41% (11, 69)
CI = confidence interval; DOR = duration of response; NE = not evaluable.

14.2 Merkel Cell Carcinoma (MCC)

The efficacy of ZYNYZ was evaluated in study POD1UM-201 (NCT03599713), an open-label, multiregional, single-arm study in 101 patients with metastatic or recurrent locally advanced MCC who had not received prior systemic therapy for their advanced disease. Patients with active autoimmune disease or a medical condition that required immunosuppression were ineligible. Patients who were HIV-positive, with an undetectable viral load, a CD4+ count ≥ 300 cells/microliter and receiving antiretroviral therapy were eligible.

Patients received ZYNYZ 500 mg intravenously every 4 weeks until disease progression, unacceptable toxicity, or up to 24 months. Tumor response assessments were performed every 8 weeks for the first year of therapy and 12 weeks thereafter.

The major efficacy outcomes were ORR and DOR as assessed by an IRC according to RECIST v1.1.

The median age of enrolled patients was 71 years (range: 38-90); 39% were ≥ 75 years; 67% of patients were male; 77% of patients were White, 1% were Asian, race was not reported in 22% of patients; 1% were Hispanic, 74% were non-Hispanic, ethnicity was not reported in 25% of patients; 73% had an ECOG performance status of 0 and 27% had an ECOG performance status of 1; 1 patient was HIV-positive. Sixty-eight percent of patients had prior surgery and 37% of patients had prior radiotherapy. Ninety percent of patients had metastatic disease at baseline. Merkel cell polyomavirus (MCPyV) was detected in 76% of evaluable biopsy samples.

Efficacy results are summarized in Table 11.

Table 11: Efficacy Results from Study POD1UM-201
Endpoint | ZYNYZ (N = 101)
Objective Response Rate (95% CI) | 55% (44, 64)
Complete responses, n (%) | 18 (18)
Partial responses, n (%) | 37 (37)
Duration of Response | N = 55
Range, months | 1.1 to 55.3+
Patients with DOR ≥ 12 months, n (%) | 38 (69)
Patients with DOR ≥ 24 months, n (%) | 25 (46)
CI = confidence interval; DOR = duration of response; + denotes ongoing response.

16 HOW SUPPLIED/STORAGE AND HANDLING

ZYNYZ (retifanlimab-dlwr) injection is a clear to slightly opalescent, colorless to pale yellow solution. It is supplied in a carton containing one single-dose vial of:

- 500 mg/20 mL (25 mg/mL) (NDC 50881-006-03)

Store refrigerated at 2°C to 8°C (36°F to 46°F) in the original carton to protect from light. Do not freeze or shake.

17 PATIENT COUNSELING INFORMATION

Advise the patient to read the FDA-approved patient labeling (Medication Guide).

Immune-Mediated Adverse Reactions

Advise patients that ZYNYZ can cause immune-mediated adverse reactions, including the following [see Warnings and Precautions (5.1)]:

- Pneumonitis: Advise patients to contact their healthcare provider immediately for signs or symptoms of pneumonitis, including new or worsening symptoms of cough, chest pain, or shortness of breath.
- Colitis: Advise patients to contact their healthcare provider immediately for signs or symptoms of colitis, including diarrhea, blood or mucus in stools, or severe abdominal pain.
- Hepatitis: Advise patients to contact their healthcare provider immediately for signs or symptoms of hepatitis.
- Endocrinopathies: Advise patients to contact their healthcare provider immediately for signs or symptoms of hypothyroidism, hyperthyroidism, adrenal insufficiency, hypophysitis, or type 1 diabetes mellitus.
- Nephritis: Advise patients to contact their healthcare provider immediately for signs or symptoms of nephritis.
- Dermatologic Adverse Reactions: Advise patients to contact their healthcare provider immediately if they develop a new rash.
- Other immune-mediated adverse reactions:
  - Advise patients that immune-mediated adverse reactions can occur and may involve any organ system, and to contact their healthcare provider immediately for any new or worsening signs or symptoms [see Warnings and Precautions (5.1)].
  - Advise patients of the risk of solid organ transplant rejection and other transplant (including corneal graft) rejection [see Warnings and Precautions (5.1)].

Infusion-Related Reactions

Advise patients to contact their healthcare provider immediately for signs or symptoms of infusion-related reactions [see Warnings and Precautions (5.2)].

Complications of Allogeneic HSCT or Solid Organ Transplant Rejection

Advise patients to contact their healthcare provider immediately if they develop signs or symptoms of post-allogeneic HSCT complications. [see Warnings and Precautions (5.3)].

Embryo-Fetal Toxicity

Advise females of reproductive potential that ZYNYZ can cause harm to a fetus and to inform their healthcare provider of a known or suspected pregnancy [see Warnings and Precautions (5.4) and Use in Specific Populations (8.1, 8.3)].

Advise females of reproductive potential to use effective contraception during treatment and for 4 months after the last dose of ZYNYZ [see Use in Specific Populations (8.3)].

Lactation

Advise female patients not to breastfeed while taking ZYNYZ and for 4 months after the last dose [see Use in Specific Populations (8.2)].

Manufactured by:
Incyte Corporation
Wilmington, DE 19803
U.S. License No. 2228

ZYNYZ and the ZYNYZ logo are registered trademarks of Incyte.
Patent Information: www.incyte.com/patents
© 2025 Incyte Corporation. All rights reserved.

MEDICATION GUIDE
ZYNYZ® (ZYE-niz)
(retifanlimab-dlwr)
injection

What is the most important information I should know about ZYNYZ?

ZYNYZ is a medicine that may treat certain types of cancers by working with your immune system. ZYNYZ can cause your immune system to attack normal organs and tissues in any area of your body and can affect the way they work. These problems can sometimes become severe or life-threatening and can lead to death. You can have more than one of these problems at the same time. These problems may happen anytime during treatment or even after your treatment has ended.

Call or see your healthcare provider right away if you develop any new or worsening signs or symptoms, including:

Lung problems.

- cough

- shortness of breath

- chest pain

Intestinal problems.

- diarrhea (loose stools) or more frequent bowel movements than usual
- stools that are black, tarry, sticky, or have blood or mucus
- severe stomach-area (abdomen) pain or tenderness

Liver problems.

- yellowing of your skin or the whites of your eyes
- severe nausea or vomiting
- pain on the right side of your stomach area (abdomen)

- dark urine (tea colored)
- bleeding or bruising more easily than normal

Hormone gland problems.

- headaches that will not go away or unusual headaches
- eye sensitivity to light
- eye problems
- rapid heartbeat
- increased sweating
- extreme tiredness
- weight gain or weight loss
- feeling more hungry or thirsty than usual

- urinating more often than usual
- hair loss
- feeling cold
- constipation
- your voice gets deeper
- dizziness or fainting
- changes in mood or behavior, such as decreased sex drive, irritability, or forgetfulness

Kidney problems.

- decrease in your amount of urine
- blood in your urine

- swelling of your ankles
- loss of appetite

Skin problems.

- rash
- itching
- skin blistering or peeling

- painful sores or ulcers in your mouth or nose, throat, or genital area
- fever or flu-like symptoms
- swollen lymph nodes

Problems can also happen in other organs and tissues. These are not all of the signs and symptoms of immune system problems that can happen with ZYNYZ. Call or see your healthcare provider right away for any new or worsening signs or symptoms, which may include:

- chest pain, irregular heartbeat, shortness of breath, or swelling of ankles
- confusion, sleepiness, memory problems, changes in mood or behavior, stiff neck, balance problems, tingling or numbness of the arms or legs
- double vision, blurry vision, sensitivity to light, eye pain, changes in eyesight
- persistent or severe muscle pain or weakness, muscle cramps
- low red blood cells, bruising

Infusion reactions that can sometimes be severe. Signs and symptoms of infusion reactions may include:

- chills or shaking
- itching or rash
- flushing
- shortness of breath or wheezing

- dizziness
- feel like passing out
- fever
- back or neck pain

Rejection of a transplanted organ or tissue. Your healthcare provider should tell you what signs and symptoms you should report and monitor you, depending on the type of organ or tissue transplant that you have had.

Complications, including graft-versus-host disease, in people who have received a bone marrow (stem cell) transplant that uses donor stem cells (allogeneic). These complications can be serious and can lead to death. These complications may happen if you underwent transplantation either before or after being treated with ZYNYZ. Your healthcare provider will monitor you for these complications.

Getting medical treatment right away may help keep these problems from becoming more serious.Your healthcare provider will check you for these problems during your treatment with ZYNYZ. Your healthcare provider may treat you with corticosteroid or hormone replacement medicines. Your healthcare provider may also need to delay or completely stop treatment with ZYNYZ if you have severe side effects.

What is ZYNYZ?

ZYNYZ is a prescription medicine used to treat adults with:

- a type of anal cancer called squamous cell carcinoma of the anal canal (SCAC).
  - ZYNYZ may be used in combination with the chemotherapy medicines carboplatin and paclitaxel, as your first treatment, when your anal cancer:
    - has returned and cannot be removed by surgery, or
    - has spread.
  - ZYNYZ may be used alone when your anal cancer:
    - has returned or has spread, and
    - you have received chemotherapy that contains platinum, and it did not work, is no longer working, or you could not tolerate it.

- a type of skin cancer called Merkel cell carcinoma (MCC). ZYNYZ may be used alone to treat your skin cancer when it has spread or returned.

It is not known if ZYNYZ is safe and effective in children.

Before you receive ZYNYZ, tell your healthcare provider about all of your medical conditions, including if you:

- have immune system problems such as Crohn’s disease, ulcerative colitis, or lupus
- have received an organ or tissue transplant, including corneal transplant
- have received or plan to receive a stem cell transplant that uses donor stem cells (allogeneic)
- have received radiation treatment to your chest area
- have a condition that affects your nervous system, such as myasthenia gravis or Guillain-Barré syndrome
- are pregnant or plan to become pregnant. ZYNYZ can harm your unborn baby.
  Females who are able to become pregnant:
  - Your healthcare provider should do a pregnancy test before you start treatment with ZYNYZ.
  - You should use an effective method of birth control during your treatment and for 4 months after your last dose of ZYNYZ. Talk to your healthcare provider about birth control methods that you can use during this time.
  - Tell your healthcare provider right away if you become pregnant or think you may be pregnant during treatment with ZYNYZ.

- are breastfeeding or plan to breastfeed. It is not known if ZYNYZ passes into your breast milk. Do not breastfeed during treatment and for 4 months after your last dose of ZYNYZ.

Tell your healthcare provider about all the medicines you take, including prescription and over-the-counter medicines, vitamins, and herbal supplements.

How will I receive ZYNYZ?

- Your healthcare provider will give you ZYNYZ into your vein through an intravenous (IV) line over 30 minutes.
- ZYNYZ is usually given every 4 weeks.
- Your healthcare provider will decide how many treatments you will need.
- Your healthcare provider will do blood tests to check you for side effects.
- If you miss any appointments, call your healthcare provider as soon as possible to reschedule your appointment.

What are the possible side effects of ZYNYZ?

ZYNYZ can cause serious side effects. See "What is the most important information I should know about ZYNYZ?"

The most common side effects of ZYNYZ when given with the chemotherapy medicines carboplatin and paclitaxel in people with SCAC include:

- tiredness
- numbness, pain, tingling or burning in your hands or feet
- nausea
- hair loss
- diarrhea
- muscle and bone pain

- constipation
- bleeding
- rash
- vomiting
- decreased appetite
- itching
- stomach-area pain

The most common side effects of ZYNYZ when used alone in people with SCAC include:

- tiredness
- muscle and bone pain
- diarrhea
- infection
- rectal or genital-area pain
- bleeding
- urinary tract infection (UTI)
- rash
- nausea
- loss of appetite
- constipation

- stomach-area pain
- shortness of breath
- fever
- vomiting
- cough
- itching
- low levels of thyroid hormone
- headache
- decreased weight

The most common side effects of ZYNYZ when used alone in people with MCC include:

- muscle and bone pain
- tiredness
- itching
- diarrhea

- rash
- fever
- nausea
- constipation

These are not all the possible side effects of ZYNYZ.
Call your doctor for medical advice about side effects. You may report side effects to FDA at 1-800-FDA-1088.

General information about the safe and effective use of ZYNYZ.
Medicines are sometimes prescribed for purposes other than those listed in a Medication Guide. If you would like more information about ZYNYZ, talk with your healthcare provider. You can ask your healthcare provider for information about ZYNYZ that is written for health professionals.

What are the ingredients in ZYNYZ?
Active ingredient: retifanlimab-dlwr
Inactive ingredients: glacial acetic acid, polysorbate 80, sodium acetate, sucrose, and Water for Injection.
Manufactured by: Incyte Corporation, Wilmington, DE 19803
U.S. License No. 2228
ZYNYZ and the ZYNYZ logo are registered trademarks of Incyte.
© 2025 Incyte Corporation. All rights reserved.
Patent Information: www.incyte.com/patents
For more information, call 1-855-463-3463.

This Medication Guide has been approved by the U.S. Food and Drug Administration. Revised: 12/2025

ZYNYZ 500 MG/20 ML CARTON

NDC 50881-006-03
Rx Only

ZYNYZ™
retifanlimab-dlwr
Injection

500 mg/20 mL
(25 mg/mL)

For intravenous infusion after dilution.
Single-dose vial. Discard unused portion.

Dispense the enclosed Medication
Guide to the patient